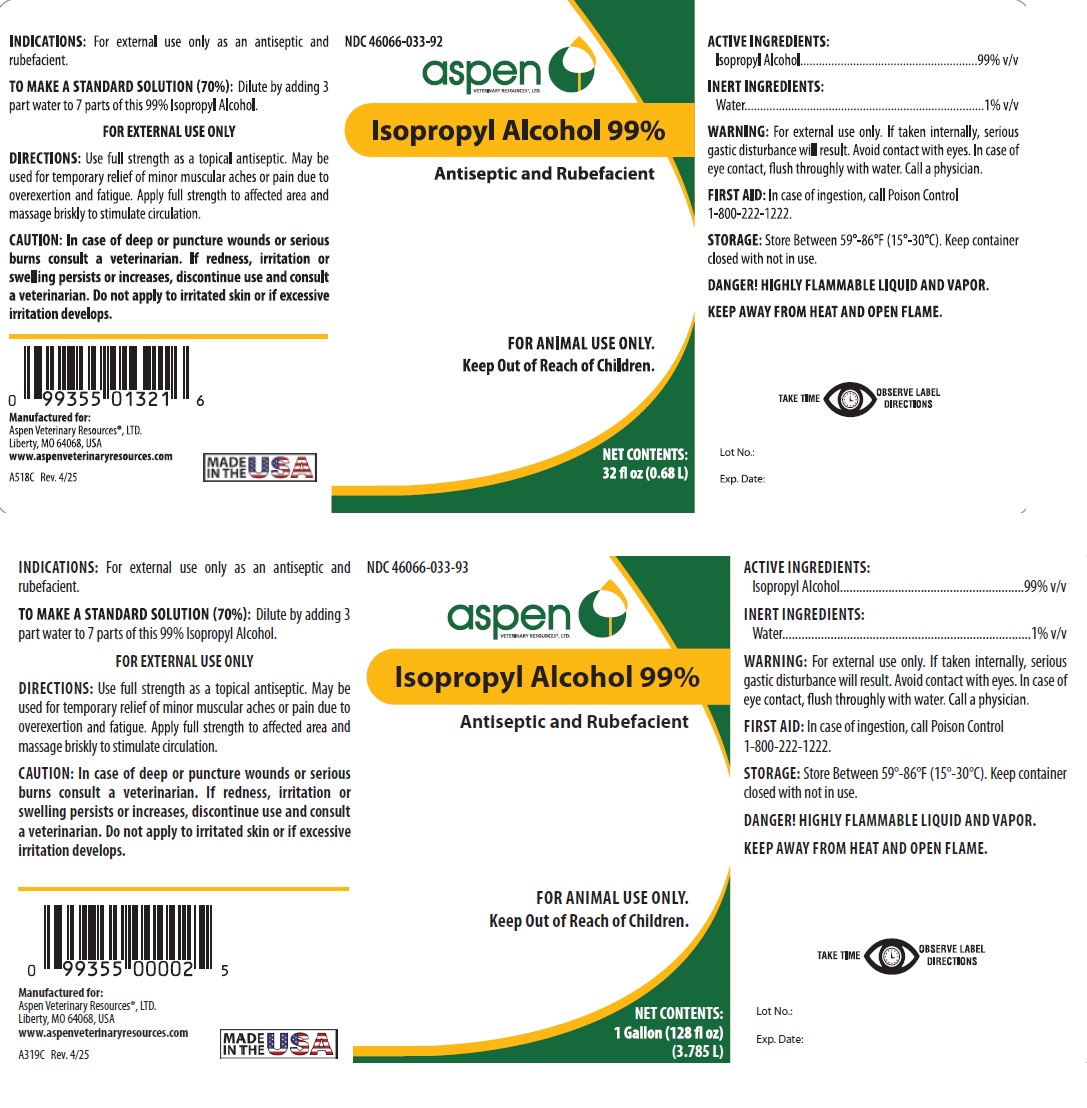 DRUG LABEL: Isopropyl Alcohol
NDC: 46066-033 | Form: LIQUID
Manufacturer: Aspen Veterinary
Category: animal | Type: OTC ANIMAL DRUG LABEL
Date: 20250415

ACTIVE INGREDIENTS: ISOPROPYL ALCOHOL 99 L/100 L
INACTIVE INGREDIENTS: WATER 1 L/100 L

WARNINGS AND PRECAUTIONS

Isopropyl Alcohol 99%

Antiseptic and Rubefacient

FOR ANIMAL USE ONLY

FOR EXTERNAL USE ONLY

Keep Out of Reach of Children

ACTIVE INGREDIENTS:

Isopropyl Alcohol ............................ 99%v/v

INACTIVE INGREDIENTS:

Water ........................................... 1%v/v

INDICATIONS: For external use only as an antiseptic and rubefacient.

TO MAKE A STANDARD SOLUTION (70%): Dilute by adding 3 part water to 7 parts of this 99% Isopropyl Alcohol.

WARNING: For external use only. If taken internally, serious gastric disturbance will result. Avoid contact with eyes. In case of eye contact, flush throughly with water. Call a physician.

FIRST AID: In case of ingestion, call Poison Control 1-800-222-1222.

STORAGE: Store Between 59°-86°F (15°-30°C). Keep container closed with not in use.

DANGER! HIGHLY FLAMMABLE LIQUID AND VAPOR.

KEEP AWAY FROM HEAT AND OPEN FLAME

DIRECTIONS: Use full strength as topical antiseptic. May be used for temporary relief of minor muscular aches or pain due to overexertion and fatigue. Apply full strength to affected area and massage briskly to stimulate circulation.

CAUTION: In case of deep or puncture wounds or serious burns, consult a veterinarian. If redness, irritation, or swelling persists or increases, discontinue use and consult a veterinarian. Do not apply to irritated skin or if excessive irritation develops.

Manufactured for:

Aspen Veterinary Resources, Ltd.

Liberty, MO 64068, USA

FC143C

Made in the USA.

Rev. 4/25